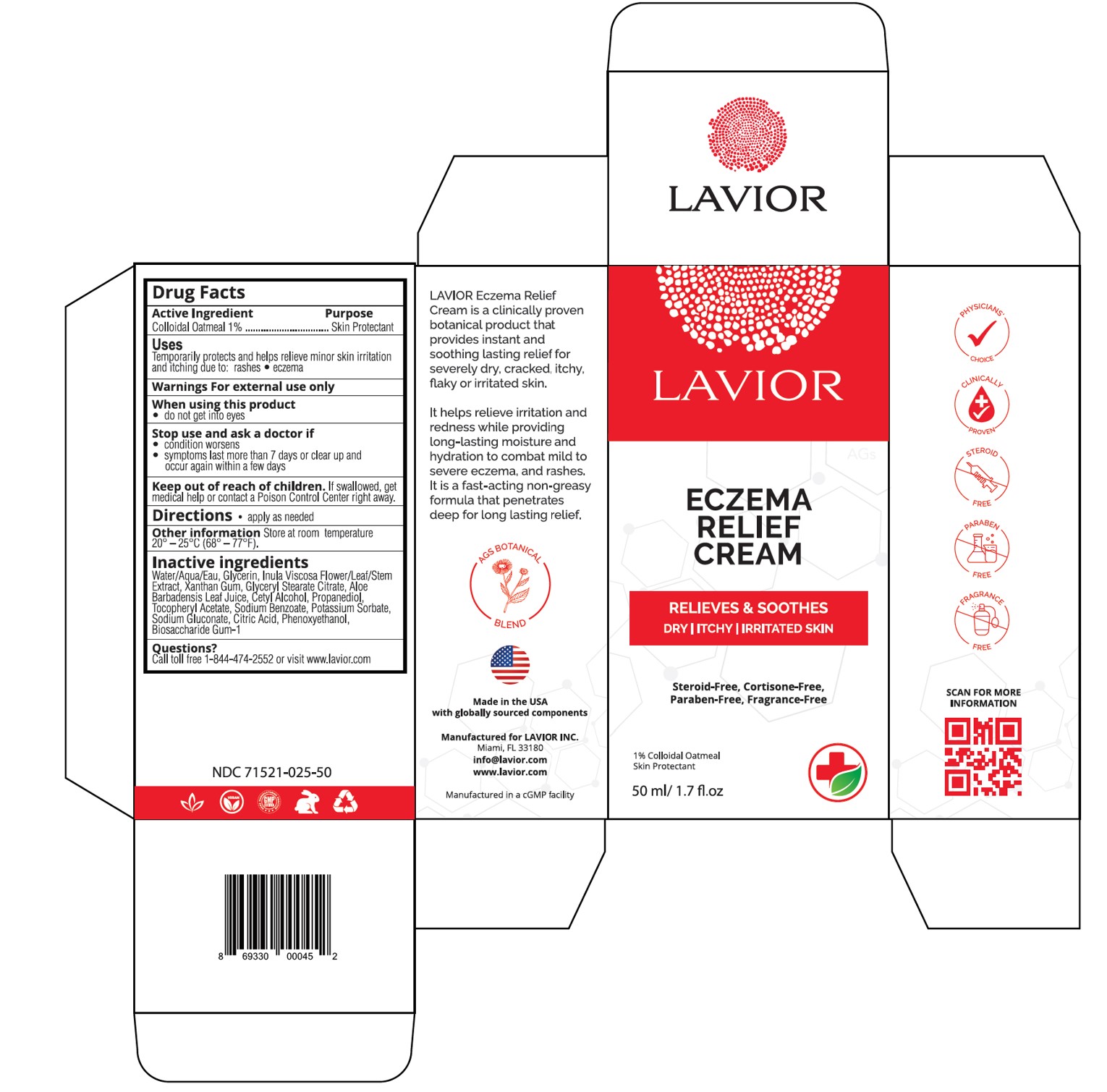 DRUG LABEL: Eczema Relief Cream
NDC: 71521-025 | Form: CREAM
Manufacturer: Lavior Pharma Inc
Category: otc | Type: HUMAN OTC DRUG LABEL
Date: 20241022

ACTIVE INGREDIENTS: OATMEAL 1 g/100 g
INACTIVE INGREDIENTS: ALOE VERA LEAF; SODIUM BENZOATE; GLYCERIN; SODIUM GLUCONATE; XANTHAN GUM; GLYCERYL STEARATE CITRATE; DITTRICHIA VISCOSA WHOLE; POTASSIUM SORBATE; CETYL ALCOHOL; BIOSACCHARIDE GUM-1; PROPANEDIOL; .ALPHA.-TOCOPHEROL ACETATE, D-; CITRIC ACID MONOHYDRATE

Active Ingredient

Colloidal Oatmeal 1%...............................Skin Protectant

Purpose

Skin Protectant

Uses

Temporarily protects and helps relieve minor skin irritation and itching due to:

- rashes
- eczema

Warnings

For external use only

When using this product

- do not get into eyes

Stop use and ask a doctor if

• condition worsens

• symptoms last more than 7 days or clear up and occur again within a few days

Keep out of reach of children

If swallowed, get medical help or contact a Poison Control Center right away.

Directions

Apply as needed

Inactive ingredients

Water/Aqua/Eau, Glyverin, Inula Viscosa Flower/Leaf/Stem Extract, Xanthan Gum, Glyceryl Stearate Citrate, Aloe Babadensis Leaf Juice, Cetyl Alcohol, Propanediol, Tocopheryl Acetate, Sodium Benzoate, Potassium Sorbate, Sodium Gluconate, Citric Acid, Phenoxyethanol, Biosaccharide Gum-A

Questions?

Call (305) 627-3680 or visit www.lavior.com